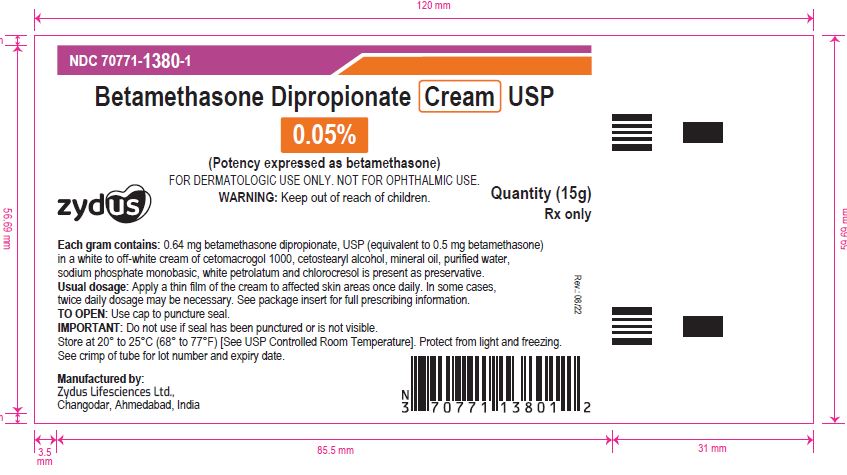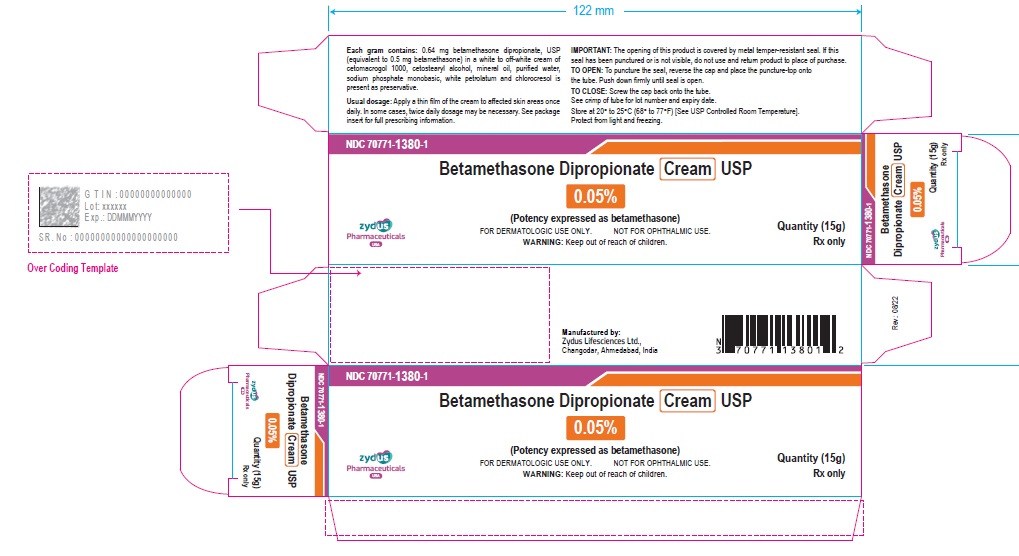 DRUG LABEL: Betamethasone dipropionate
NDC: 70771-1380 | Form: CREAM
Manufacturer: Zydus Lifesciences Limited
Category: prescription | Type: HUMAN PRESCRIPTION DRUG LABEL
Date: 20241125

ACTIVE INGREDIENTS: BETAMETHASONE DIPROPIONATE 0.5 mg/1 g
INACTIVE INGREDIENTS: CETETH-20; CETOSTEARYL ALCOHOL; CHLOROCRESOL; MINERAL OIL; PETROLATUM; SODIUM PHOSPHATE, MONOBASIC; WATER

Betamethasone Dipropionate Cream USP, 0.05%
(Potency expressed as betamethasone)
FOR DERMATOLOGIC USE ONLY.
NOT FOR OPHTHALMIC USE.

PACKAGE LABEL.PRINCIPAL DISPLAY PANEL

NDC 70771-1380-1

Betamethasone dipropionate cream USP, 0.05%

Rx only

15 g